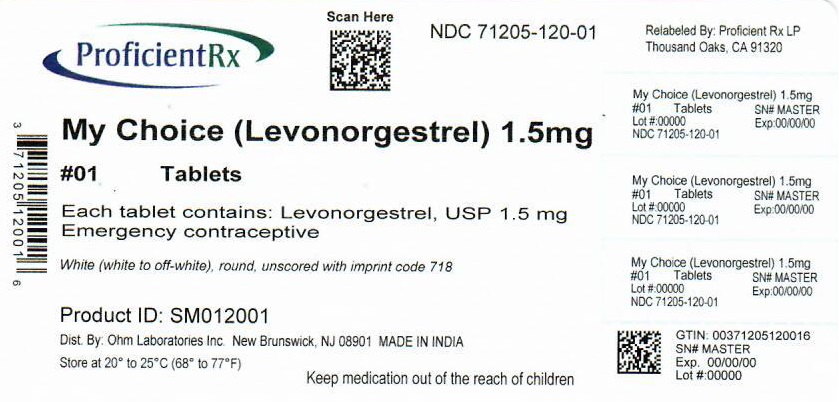 DRUG LABEL: My Choice TM
NDC: 71205-120 | Form: TABLET
Manufacturer: Proficient Rx LP
Category: otc | Type: HUMAN OTC DRUG LABEL
Date: 20220901

ACTIVE INGREDIENTS: LEVONORGESTREL 1.5 mg/1 1
INACTIVE INGREDIENTS: SILICON DIOXIDE; STARCH, CORN; HYPROMELLOSE, UNSPECIFIED; LACTOSE MONOHYDRATE; MAGNESIUM STEARATE; TALC

My Choice™

Drug Facts

Active ingredient

Levonorgestrel, USP 1.5 mg

Purpose

Emergency contraceptive

Use

for women to reduce chance of pregnancy af ter unprotected sex (if a contraceptive failed or if you did not use bir th control)

Warnings

Allergy alert

Do not use if you have ever had an allergic reaction to levonorgestrel

Sexually transmitted diseases (STDs) alert

This product does not protect against HIV/AIDS or other STDs.

Do not use

- if you are already pregnant (because it will not work)
- for regular bir th control

Ask a doctor or pharmacist before use if you are taking efavirenz (HIV medication) or rifampin (tuberculosis treatment) or medication for seizures (epilepsy). These medications may reduce the effectiveness of levonorgestrel.

When using this product you may have

- menstrual changes
- tiredness
- dizziness
- nausea
- headache
- breast pain
- lower stomach (abdominal) pain
- vomiting

Keep out of reach of children. In case of overdose, get medical help or contact a Poison Control Center right away (1-800-222-1222).

Directions

- take as soon as possible within 72 hours (3 days) after unprotected sex. The sooner you take it, the better it will work.
- if you vomit within 2 hours after taking the medication, call a healthcare professional to find out if you should repeat the dose

Other information

- read the instructions, warnings, and enclosed product leaflet before use
- this product works mainly by preventing ovulation (egg release). It may also prevent fer tilization of a released egg (joining of sperm and egg) or at tachment of a fer tilized egg to the uterus (implantation).
- do not use if carton is open or tear strip is removed or blister seal is broken or missing
- store at 20° to 25°C (68° to 77°F)

Inactive ingredients

colloidal silicon dioxide, corn starch, hypromellose, lactose monohydrate, magnesium stearate, talc

Questions or comments?

For more information, call toll free 1-800-818-4555 weekdays

Distributed by:
Ohm Laboratories Inc.
New Brunswick, NJ 08901

Relabeled by:
Proficient Rx LP
Thousand Oaks, CA 91320

PRINCIPAL DISPLAY PANEL - 1.5 mg Tablet Blister Pack Carton

† Compare To
the active ingredient of
Plan B One-Step®

NDC 71205-120-01

See New Warning

My
Choice™

Levonorgestrel Tablet 1.5 mg
Emergency Contraceptive

- Reduces the chance of pregnancy after unprotected sex
- Not for regular birth control
- The sooner you take it, the more effective it will be
- Take as soon as possible within 72 hours (3 days)
  after unprotected sex
- Will not harm an existing pregnancy

1 Tablet Levonorgestrel 1.5 mg

One Tablet. One Step.